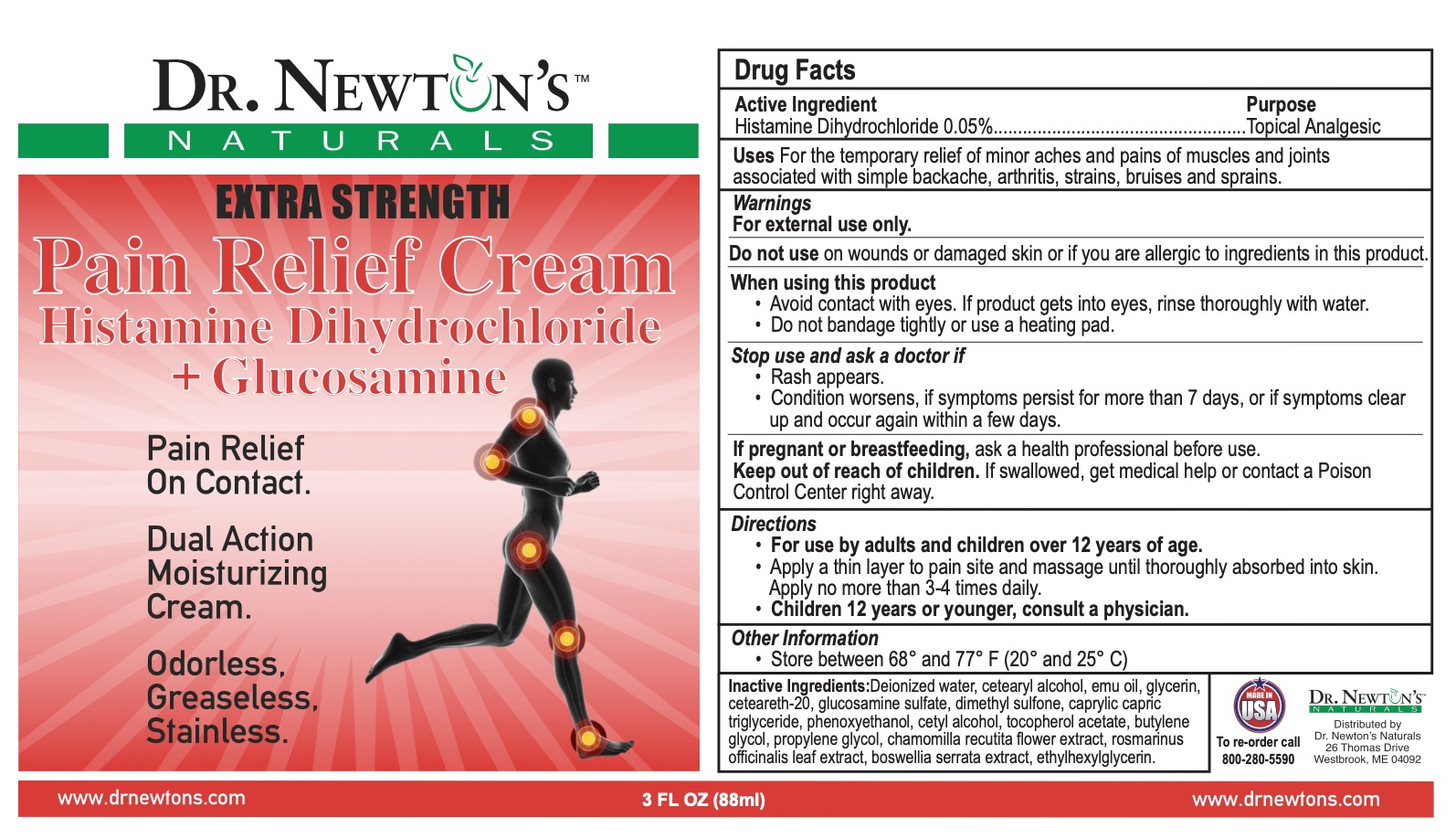 DRUG LABEL: Glucosamine Cream EXTRA STRENGTH
NDC: 78983-101 | Form: CREAM
Manufacturer: IDEAZ, LLC
Category: otc | Type: HUMAN OTC DRUG LABEL
Date: 20251212

ACTIVE INGREDIENTS: HISTAMINE DIHYDROCHLORIDE 0.05 g/100 g
INACTIVE INGREDIENTS: ETHYLHEXYLGLYCERIN; WATER; CETOSTEARYL ALCOHOL; EMU OIL; GLYCERIN; POLYOXYL 20 CETOSTEARYL ETHER; GLUCOSAMINE SULFATE; DIMETHYL SULFONE; MEDIUM-CHAIN TRIGLYCERIDES; PHENOXYETHANOL; CETYL ALCOHOL; .ALPHA.-TOCOPHEROL ACETATE; BUTYLENE GLYCOL; PROPYLENE GLYCOL; CHAMOMILE; ROSEMARY; INDIAN FRANKINCENSE

Glucosamine Cream EXTRA STRENGTH

Active Ingredient

Histamine Dihydrochloride 0.05%

Purpose

Topical Analgesic

INDICATIONS AND USAGE

Uses For the temporary relief of minor aches and pains of muscles and joints associated with simple backache, arthritis, strains, bruises and sprains

Warnings For external use only

When using this product

- Avoid contact with eyes
- Do not bandage tightly

Do not use

- On wounds or damaged skin or if you are allergic to ingredients in this product.

Discontinue use and consult a physician if: Condition worsens or if symptoms persists for more than 7 days or clear up and occur again within a few days

Keep out of reach of children.

If swallowed get medical help or contact a poison control center

Directions

For use by adults and children over 12 years:

Apply to affected area not more than 3 to 4 times daily.

INACTIVE INGREDIENT

Inactive ingredients Deionized water, cetearyl alcohol, emu oil, glycerin, ceteareth-20, glucosamine sulfate, dimethyl sulfone, caprylic capric triglyceride, phenoxyethanol, cetyl alcohol, tocopherol acetate, butylene glycol, propylene glycol, chamomilla recutita flower extract, rosmarinus officinalis leaf extract, boswellia serrata extract, ethylhexylglycerin

Pain Relief On Contact

Dual Action Moisturizing Cream

Odorless, Greaseless, Stainless.

Made in USA

For re-orders call 800-280-5590

www.drnewtons.com

Distributed by

Dr. Newton's Naturals

26 Thomas Drive

Westbrook, ME 04092